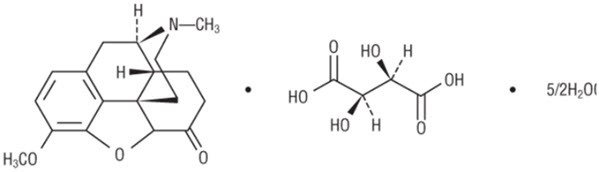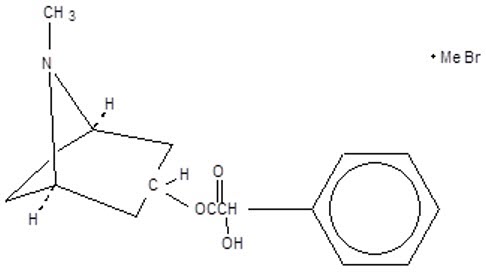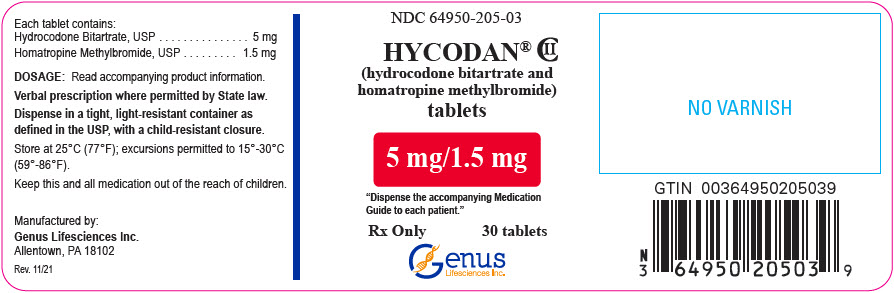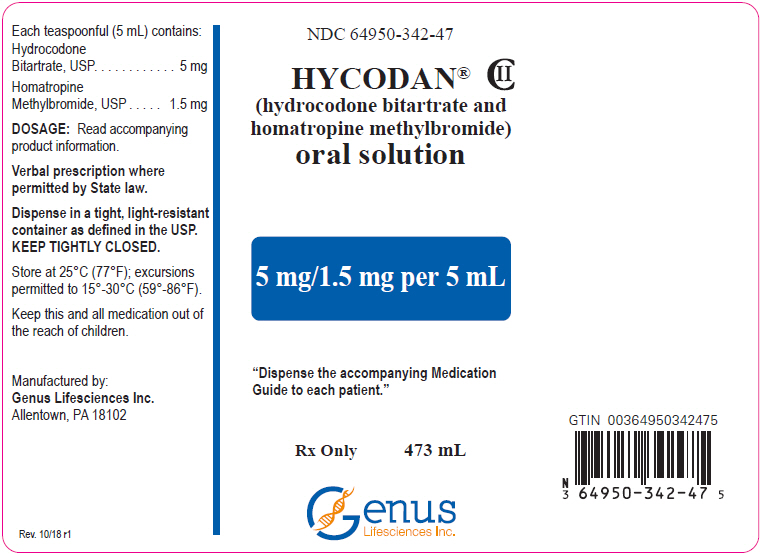 DRUG LABEL: Hycodan
NDC: 64950-205 | Form: TABLET
Manufacturer: Genus Lifesciences Inc.
Category: prescription | Type: HUMAN PRESCRIPTION DRUG LABEL
Date: 20240109
DEA Schedule: CII

ACTIVE INGREDIENTS: hydrocodone bitartrate 5 mg/1 1; homatropine methylbromide 1.5 mg/1 1
INACTIVE INGREDIENTS: Silicon Dioxide; Dibasic Calcium Phosphate Dihydrate; Lactose Monohydrate; Starch, Corn; Stearic Acid; Magnesium Stearate

HIGHLIGHTS OF PRESCRIBING INFORMATION

These highlights do not include all the information needed to use HYCODAN® safely and effectively. See full prescribing information for HYCODAN.
HYCODAN (hydrocodone bitartrate and homatropine methylbromide) tablets, for oral use, CII
HYCODAN (hydrocodone bitartrate and homatropine methylbromide) oral solution, CII
Initial U.S. Approval: 1943

WARNING: ADDICTION, ABUSE, AND MISUSE; LIFE-THREATENING RESPIRATORY DEPRESSION; ACCIDENTAL INGESTION; MEDICATION ERRORS; CYTOCHROME P450 3A4 INTERACTION; CONCOMITANT USE WITH BENZODIAZEPINES OR OTHER CNS DEPRESSANTS; INTERACTION WITH ALCOHOL; NEONATAL OPIOID WITHDRAWAL SYNDROME

See full prescribing information for complete boxed warning.

- HYCODAN exposes users to risks of addiction, abuse, and misuse, which can lead to overdose and death. Assess patient's risk before prescribing and monitor closely for these behaviors and conditions. (5.1)
- Serious, life-threatening, or fatal respiratory depression may occur. Monitor closely, especially upon initiation or when used in patients at higher risk. (5.2)
- Accidental ingestion of HYCODAN, especially by children, can result in a fatal overdose of hydrocodone. (5.2)
- Ensure accuracy when prescribing, dispensing, and administering HYCODAN. Dosing errors can result in accidental overdose and death. (2.1, 5.5)
- Concomitant use with CYP3A4 inhibitors (or discontinuation of CYP3A4 inducers) can result in a fatal overdose of hydrocodone. Avoid the use of HYCODAN in patients taking CYP3A4 inhibitors or inducers. (5.7, 7.2, 7.3)
- Concomitant use of opioids with benzodiazepines or other central nervous system (CNS) depressants, including alcohol, may result in profound sedation, respiratory depression, coma, and death. Avoid the use of HYCODAN in patients taking benzodiazepines, other CNS depressants, or alcohol. (5.8, 7.4)
- Instruct patients not to consume alcohol or any products containing alcohol while taking HYCODAN because co-ingestion can result in fatal plasma hydrocodone levels. (5.8, 7.1)
- HYCODAN is not recommended for use in pregnant women. Prolonged use of HYCODAN during pregnancy can result in neonatal opioid withdrawal syndrome, which may be life-threatening if not recognized and treated. If HYCODAN is used for a prolonged period in a pregnant woman, advise the patient of the risk of neonatal opioid withdrawal syndrome and ensure that appropriate treatment will be available. (5.13, 8.1)

1 INDICATIONS AND USAGE

HYCODAN is a combination of hydrocodone, an opioid agonist; and homatropine, a muscarinic antagonist, indicated for the symptomatic relief of cough in adult patients 18 years of age and older. (1)

Limitations of Use (1)

- Not indicated for pediatric patients under 18 years of age.
- Because of the risks of addiction, abuse, and misuse with opioids, even at recommended doses, reserve HYCODAN for use in adult patients for whom the benefits of cough suppression are expected to outweigh the risks, and in whom an adequate assessment of the etiology of the cough has been made.

2 DOSAGE AND ADMINISTRATION

- Adults 18 years of age and older: One (1) tablet or 5 mL of the oral solution every 4 to 6 hours as needed; not to exceed six (6) tablets or 30 mL in 24 hours. (2.2)
- Measure HYCODAN oral solution with an accurate milliliter measuring device. (2.1, 5.5)
- Do not increase the dose or dosing frequency. (2.1)
- Prescribe for the shortest duration consistent with treatment goals. (2.3)
- Reevaluate patients with unresponsive cough in 5 days or sooner for possible underlying pathology. (2.3)
- Reevaluate patient prior to refilling. (2.3)

3 DOSAGE FORMS AND STRENGTHS

- Tablets: 5 mg of hydrocodone bitartrate and 1.5 mg of homatropine methylbromide per tablet. (3)
- Oral solution: 5 mg of hydrocodone bitartrate and 1.5 mg of homatropine methylbromide per 5 mL. (3)

4 CONTRAINDICATIONS

- Children younger than 6 years of age. (4)
- Significant respiratory depression. (4)
- Acute or severe bronchial asthma in an unmonitored setting or in absence of resuscitative equipment. (4)
- Known or suspected gastrointestinal obstruction, including paralytic ileus. (4)
- Hypersensitivity to hydrocodone, homatropine, or any of the inactive ingredients in HYCODAN. (4)

5 WARNINGS AND PRECAUTIONS

- Life-threatening respiratory depression in patients with chronic pulmonary disease or in elderly, cachectic, or debilitated patients: Monitor closely, particularly during initiation of therapy. (5.4)
- Activities requiring mental alertness: Avoid engaging in hazardous tasks requiring mental alertness such as driving or operating machinery. (5.6)
- Risks of use in patients with head injury, impaired consciousness, increased intracranial pressure, or brain tumors: Avoid use. May increase intracranial pressure and obscure the clinical course of head injuries. (5.10)
- Seizures in patients with seizure disorders: Monitor during therapy. (5.11)
- Severe hypotension: Monitor during initiation of therapy. Avoid use in patients with circulatory shock. (5.12)
- Adrenal insufficiency: If diagnosed, treat with physiologic replacement of corticosteroids, and wean patient off of the opioid. (5.14)

6 ADVERSE REACTIONS

Common adverse reactions include: Sedation (somnolence, mental clouding, lethargy), impaired mental and physical performance, lightheadedness, dizziness, headache, dry mouth, nausea, vomiting, and constipation. (6)

To report SUSPECTED ADVERSE REACTIONS, contact Allucent at 1-866-511-6754 or FDA at 1-800-FDA-1088 or www.fda.gov/medwatch.

7 DRUG INTERACTIONS

- Serotonergic Drugs: Concomitant use may result in serotonin syndrome. Discontinue if serotonin syndrome is suspected. (7.5)
- Monoamine Oxidase Inhibitors (MAOIs): Can potentiate the effects of hydrocodone. Avoid concomitant use in patients receiving MAOIs or within 14 days of stopping an MAOI. (7.6)
- Muscle Relaxants: Avoid concomitant use. (7.7)
- Diuretics: Hydrocodone may reduce the efficacy of diuretics. Monitor for reduced effect. (7.8)
- Anticholinergic drugs: Concurrent use may cause paralytic ileus. (5.9, 7.9)

8 USE IN SPECIFIC POPULATIONS

- Pregnancy: Avoid use in pregnant women. May cause fetal harm. (8.1)
- Lactation: Breastfeeding not recommended. (8.2)
- Renal Impairment: Use with caution in patients with severe renal impairment. (8.6)
- Hepatic Impairment: Use with caution in patients with severe hepatic impairment. (8.7)

FULL PRESCRIBING INFORMATION

WARNING: ADDICTION, ABUSE, AND MISUSE; LIFE-THREATENING RESPIRATORY DEPRESSION; ACCIDENTAL INGESTION; MEDICATION ERRORS; CYTOCHROME P450 3A4 INTERACTION; CONCOMITANT USE WITH BENZODIAZEPINES OR OTHER CNS DEPRESSANTS; INTERACTION WITH ALCOHOL; NEONATAL OPIOID WITHDRAWAL SYNDROME

Addiction, Abuse, and Misuse

HYCODAN exposes patients and other users to the risks of opioid addiction, abuse, and misuse, which can lead to overdose and death. Reserve HYCODAN for use in adult patients for whom the benefits of cough suppression are expected to outweigh the risks, and in whom an adequate assessment of the etiology of the cough has been made. Assess each patient's risk prior to prescribing HYCODAN, prescribe HYCODAN for the shortest duration that is consistent with individual patient treatment goals, monitor all patients regularly for the development of addiction or abuse, and refill only after reevaluation of the need for continued treatment [see Warnings and Precautions (5.1)].

Life-Threatening Respiratory Depression

Serious, life-threatening, or fatal respiratory depression may occur with use of HYCODAN. Monitor for respiratory depression, especially during initiation of HYCODAN therapy or when used in patients at higher risk [see Warnings and Precautions (5.2)].

Accidental Ingestion

Accidental ingestion of even one dose of HYCODAN, especially by children, can result in a fatal overdose of hydrocodone [see Warnings and Precautions (5.2)].

Risk of Medication Errors

Ensure accuracy when prescribing, dispensing, and administering HYCODAN. Dosing errors can result in accidental overdose and death. Always use an accurate milliliter measuring device when measuring and administering HYCODAN [see Dosage and Administration (2.1), Warnings and Precautions (5.5)].

Cytochrome P450 3A4 Interaction

The concomitant use of HYCODAN with all cytochrome P450 3A4 inhibitors may result in an increase in hydrocodone plasma concentrations, which could increase or prolong adverse drug effects and may cause potentially fatal respiratory depression. In addition, discontinuation of a concomitantly used cytochrome P450 3A4 inducer may result in an increase in hydrocodone plasma concentration. Avoid the use of HYCODAN in patients taking a CYP3A4 inhibitor or inducer [see Warnings and Precautions (5.7), Drug Interactions (7.2, 7.3)].

Risks from Concomitant Use with Benzodiazepines or Other CNS Depressants

Concomitant use of opioids with benzodiazepines or other central nervous system (CNS) depressants, including alcohol, may result in profound sedation, respiratory depression, coma, and death. Avoid the use of HYCODAN in patients taking benzodiazepines, other CNS depressants, or alcohol [see Warnings and Precautions (5.8), Drug Interactions (7.5)].

Interaction with Alcohol

Instruct patients not to consume alcoholic beverages or use prescription or non-prescription products that contain alcohol while taking HYCODAN. The co-ingestion of alcohol with HYCODAN may result in increased plasma levels and a potentially fatal overdose of hydrocodone [see Warnings and Precautions (5.8), Drug Interactions (7.1)].

Neonatal Opioid Withdrawal Syndrome

HYCODAN is not recommended for use in pregnant women [see Use in Specific Populations (8.1)]. Prolonged use of HYCODAN during pregnancy can result in neonatal opioid withdrawal syndrome, which may be life-threatening if not recognized and treated, and requires management according to protocols developed by neonatology experts. If HYCODAN is used for a prolonged period in a pregnant woman, advise the patient of the risk of neonatal opioid withdrawal syndrome and ensure that appropriate treatment will be available [see Warnings and Precautions (5.13)].

1 INDICATIONS AND USAGE

HYCODAN is indicated for the symptomatic relief of cough in adult patients 18 years of age and older.

Limitations of Use:

- Not indicated for pediatric patients under 18 years of age [see Use in Specific Populations (8.4)].
- Contraindicated in pediatric patients less than 6 years of age [see Contraindications (4)].
- Because of the risks of addiction, abuse, and misuse with opioids, even at recommended doses [see Warnings and Precautions (5.1)], reserve HYCODAN for use in adult patients for whom the benefits of cough suppression are expected to outweigh the risks, and in whom an adequate assessment of the etiology of the cough has been made.

2 DOSAGE AND ADMINISTRATION

2.1 Important Dosage and Administration Instructions

Administer HYCODAN by the oral route only.

Always use an accurate milliliter measuring device when administering HYCODAN oral solution to ensure that the dose is measured and administered accurately. A household teaspoon is not an accurate measuring device and could lead to overdosage [see Warnings and Precautions (5.5)]. For prescriptions where a measuring device is not provided, a pharmacist can provide an appropriate measuring device and can provide instructions for measuring the correct dose. Do not overfill. Rinse the measuring device with water after each use.

Advise patients not to increase the dose or dosing frequency of HYCODAN because serious adverse events such as respiratory depression may occur with overdosage [see Warnings and Precautions (5.2), Overdosage (10)]. The dosage of HYCODAN should not be increased if cough fails to respond; an unresponsive cough should be reevaluated for possible underlying pathology [see Dosage and Administration (2.3), Warnings and Precautions (5.4)].

2.2 Recommended Dosage

Adults 18 years of age and older: One (1) tablet or 5 mL of the oral solution every 4 to 6 hours as needed; not to exceed six (6) tablets or 30 mL in 24 hours.

2.3 Monitoring, Maintenance, and Discontinuation of Therapy

- Prescribe HYCODAN for the shortest duration that is consistent with individual patient treatment goals [see Warnings and Precautions (5.1)].
- Monitor patients closely for respiratory depression, especially within the first 24 to72 hours of initiating therapy [see Warnings and Precautions (5.2)].
- Reevaluate patients with unresponsive cough in 5 days or sooner for possible underlying pathology, such as foreign body or lower respiratory tract disease [see Warnings and Precautions (5.4)]. If a patient requires a refill, reevaluate the cause of the cough and assess the need for continued treatment with HYCODAN, the relative incidence of adverse reactions, and the development of addiction, abuse, or misuse [see Warnings and Precautions (5.1)].
- Do not abruptly discontinue HYCODAN in a physically-dependent patient [see Drug Abuse and Dependence (9.3)]. When a patient who has been taking HYCODAN regularly and may be physically dependent no longer requires therapy with HYCODAN, taper the dose gradually, by 25% to 50% every 2 to 4 days, while monitoring carefully for signs and symptoms of withdrawal. If the patient develops these signs or symptoms, raise the dose to the previous level and taper more slowly, either by increasing the interval between decreases, decreasing the amount of change in dose, or both.

3 DOSAGE FORMS AND STRENGTHS

- Tablets: 5 mg of hydrocodone bitartrate and 1.5 mg of homatropine methylbromide per tablet, white-colored, biconvex, one face bisected and debossed with "205", and the other face plain [see Description (11)].
- Oral solution: 5 mg of hydrocodone bitartrate and 1.5 mg of homatropine methylbromide per 5 mL, a clear red-colored, cherry-flavored [see Description (11)].

4 CONTRAINDICATIONS

HYCODAN is contraindicated for:

- All pediatric patients younger than 6 years of age [see Warnings and Precautions (5.2, 5.3), Use in Specific Populations (8.4)].
- Significant respiratory depression [see Warnings and Precautions (5.2)].
- Acute or severe bronchial asthma in an unmonitored setting or in the absence of resuscitative equipment [see Warnings and Precautions (5.4)].
- Known or suspected gastrointestinal obstruction, including paralytic ileus [see Warnings and Precautions (5.9)].
- Hypersensitivity to hydrocodone, homatropine, or any of the inactive ingredients in HYCODAN [see Adverse Reactions (6)].

5 WARNINGS AND PRECAUTIONS

5.1 Addiction, Abuse, and Misuse

- HYCODAN contains hydrocodone, a Schedule II controlled substance. As an opioid, HYCODAN exposes users to the risks of addiction, abuse, and misuse [see Drug Abuse and Dependence (9)], which can lead to overdose and death [see Overdosage (10)].
- Reserve HYCODAN for use in adult patients for whom the benefits of cough suppression are expected to outweigh the risks, and in whom an adequate assessment of the etiology of the cough has been made.
- Assess each patient's risk prior to prescribing HYCODAN, prescribe HYCODAN for the shortest duration that is consistent with individual patient treatment goals, monitor all patients regularly for the development of addiction or abuse, and refill only after reevaluation of the need for continued treatment.
- Although the risk of addiction in any individual is unknown, it can occur in patients appropriately prescribed HYCODAN. Addiction can occur at recommended dosages and if the drug is misused or abused. Risks are increased in patients with a personal or family history of substance abuse (including drug or alcohol abuse or addiction) or mental illness (e.g., major depression).
- Opioids are sought by drug abusers and people with addiction disorders and are subject to criminal diversion. Consider these risks when prescribing or dispensing HYCODAN. Strategies to reduce these risks include prescribing the drug in the smallest appropriate quantity and advising the patient on the proper disposal of unused drug [see Patient Counseling Information (17)]. Contact local state professional licensing board or state controlled substances authority for information on how to prevent and detect abuse or diversion of this product.

5.2 Life-Threatening Respiratory Depression

- Serious, life-threatening, or fatal respiratory depression has been reported with the use of opioids, including hydrocodone, one of the active ingredients in HYCODAN. Hydrocodone produces dose-related respiratory depression by directly acting on the brain stem respiratory center that controls respiratory rhythm and may produce irregular and periodic breathing. Respiratory depression, if not immediately recognized and treated, may lead to respiratory arrest and death. Management of respiratory depression includes discontinuation of HYCODAN, close observation, supportive measures, and use of opioid antagonists (e.g., naloxone), depending on the patient's clinical status [see Overdosage (10)]. Carbon dioxide (CO2) retention from opioid-induced respiratory depression can exacerbate the sedating effects of opioids.
- While serious, life-threatening, or fatal respiratory depression can occur at any time during the use of HYCODAN, the risk is greatest during the initiation of therapy, when HYCODAN is used concomitantly with other drugs that may cause respiratory depression [see Warnings and Precautions (5.8)], in patients with chronic pulmonary disease or decreased respiratory reserve, and in patients with altered pharmacokinetics or altered clearance (e.g., elderly, cachectic, or debilitated patients) [see Warnings and Precautions (5.4)].
- To reduce the risk of respiratory depression, proper dosing of HYCODAN is essential [see Dosage and Administration (2.1), Warnings and Precautions (5.5)]. Monitor patients closely, especially within the first 24 to 72 hours of initiating therapy or when used in patients at higher risk.
- Overdose of hydrocodone in adults has been associated with fatal respiratory depression, and the use of hydrocodone in pediatric patients younger than 6 years of age has been associated with fatal respiratory depression when used as recommended. Accidental ingestion of even one dose of HYCODAN, especially by children, can result in respiratory depression and death.

5.3 Risks with Use in Pediatric Populations

- Pediatric patients are particularly sensitive to the respiratory depressant effects of hydrocodone [see Warnings and Precautions (5.2)]. Because of the risk of life-threatening respiratory depression and death, HYCODAN is contraindicated in pediatric patients less than 6 years of age [see Contraindications (4)].
- Use of HYCODAN in pediatric patients also exposes them to the risks of addiction, abuse, and misuse [see Drug Abuse and Dependence (9)], which can lead to overdose and death [see Warnings and Precautions (5.1), Overdosage (10)]. Because the benefits of symptomatic treatment of cough associated with allergies or the common cold do not outweigh the risks of use of hydrocodone in pediatric patients, HYCODAN is not indicated for use in patients younger than 18 years of age [see Indications (1), Use in Specific Populations (8.4)].

5.4 Risks with Use in Other At-Risk Populations

Unresponsive Cough

The dosage of HYCODAN should not be increased if cough fails to respond; an unresponsive cough should be reevaluated in 5 days or sooner for possible underlying pathology, such as foreign body or lower respiratory tract disease [see Dosage and Administration (2.3)].

Asthma and Other Pulmonary Disease

- The use of HYCODAN in patients with acute or severe bronchial asthma in an unmonitored setting or in the absence of resuscitative equipment is contraindicated [see Contraindications (4)].
- Opioid analgesics and antitussives, including hydrocodone, one of the active ingredients in HYCODAN, should not be used in patients with acute febrile illness associated with productive cough or in patients with chronic respiratory disease where interference with ability to clear the tracheobronchial tree of secretions would have a deleterious effect on the patient's respiratory function.
- HYCODAN-treated patients with significant chronic obstructive pulmonary disease or cor pulmonale, and those with a substantially decreased respiratory reserve, hypoxia, hypercapnia, or pre-existing respiratory depression are at increased risk of decreased respiratory drive including apnea, even at recommended dosages of HYCODAN [see Warnings and Precautions (5.2)].

Elderly, Cachectic, or Debilitated Patients

- Life-threatening respiratory depression is more likely to occur in elderly, cachectic, or debilitated patients because they may have altered pharmacokinetics or altered clearance compared to younger, healthier patients [see Warnings and Precautions (5.2)].
- Because of the risk of respiratory depression, avoid the use of opioid antitussives, including HYCODAN in patients with compromised respiratory function, patients at risk of respiratory failure, and in elderly, cachectic, or debilitated patients. If HYCODAN is prescribed, monitor such patients closely, particularly when initiating HYCODAN and when HYCODAN is given concomitantly with other drugs that depress respiration [see Warnings and Precautions (5.8)].

5.5 Risk of Accidental Overdose and Death due to Medication Errors

- Dosing errors can result in accidental overdose and death. To reduce the risk of overdose and respiratory depression, ensure that the dose of HYCODAN is communicated clearly and dispensed accurately [see Dosage and Administration (2.1)].
- Advise patients to always use an accurate milliliter measuring device when measuring and administering HYCODAN oral solution. Inform patients that household teaspoon is not an accurate measuring device and such use could lead to overdosage and serious adverse reactions [see Overdosage (10)]. For prescriptions where a measuring device is not provided, a pharmacist can provide an appropriate calibrated measuring device and can provide instructions for measuring the correct dose.

5.6 Activities Requiring Mental Alertness: Risks of Driving and Operating Machinery

Hydrocodone, one of the active ingredients in HYCODAN, may produce marked drowsiness and impair the mental and/or physical abilities required for the performance of potentially hazardous tasks such as driving a car or operating machinery. Advise patients to avoid engaging in hazardous tasks requiring mental alertness and motor coordination after ingestion of HYCODAN. Avoid concurrent use of HYCODAN with alcohol or other central nervous system depressants because additional impairment of central nervous system performance may occur [see Warnings and Precautions (5.8)].

5.7 Risks from Concomitant Use or Discontinuation of Cytochrome P450 3A4 Inhibitors and Inducers

- Concomitant use of HYCODAN with a CYP3A4 inhibitor, such as macrolide antibiotics (e.g., erythromycin), azole-antifungal agents (e.g., ketoconazole), and protease inhibitors (e.g., ritonavir), may increase plasma concentrations of hydrocodone and prolong opioid adverse reactions, which may cause potentially fatal respiratory depression [see Warnings and Precautions (5.2)], particularly when an inhibitor is added after a stable dose of HYCODAN is achieved. Similarly, discontinuation of a CYP3A4 inducer, such as rifampin, carbamazepine, and phenytoin, in HYCODAN-treated patients may increase hydrocodone plasma concentrations and prolong opioid adverse reactions.
- Concomitant use of HYCODAN with CYP3A4 inducers or discontinuation of a CYP3A4 inhibitor could decrease hydrocodone plasma concentrations, decrease opioid efficacy or, possibly, lead to a withdrawal syndrome in a patient who had developed physical dependence to hydrocodone.
- Avoid the use of HYCODAN in patients who are taking a CYP3A4 inhibitor or inducer. If concomitant use of HYCODAN with a CYP3A4 inhibitor or inducer is necessary, monitor patients for signs and symptoms that may reflect opioid toxicity and opioid withdrawal [see Drug Interactions (7.2, 7.3)].

5.8 Risks from Concomitant Use with Benzodiazepines or other CNS Depressants

- Concomitant use of opioids, including HYCODAN, with benzodiazepines, or other CNS depressants, including alcohol, may result in profound sedation, respiratory depression, coma, and death. Because of these risks, avoid use of opioid cough medications in patients taking benzodiazepines, other CNS depressants, or alcohol [see Drug Interactions (7.1, 7.4)].
- Observational studies have demonstrated that concomitant use of opioid analgesics and benzodiazepines increases the risk of drug-related mortality compared to use of opioids alone. Because of similar pharmacologic properties, it is reasonable to expect similar risk with concomitant use of opioid cough medications and benzodiazepines, other CNS depressants, or alcohol.
- Advise both patients and caregivers about the risks of respiratory depression and sedation if HYCODAN is used with benzodiazepines, alcohol, or other CNS depressants [see Patient Counseling Information (17)].
- Patients must not consume alcoholic beverages, or prescription or non-prescription products containing alcohol, while on HYCODAN therapy. The co-ingestion of alcohol with HYCODAN may result in increased plasma levels and a potentially fatal overdose of hydrocodone [see Drug Interactions (7.1)].

5.9 Risks of Use in Patients with Gastrointestinal Conditions

- HYCODAN is contraindicated in patients with known or suspected gastrointestinal obstruction, including paralytic ileus [see Contraindications (4)]. The use of hydrocodone in HYCODAN may obscure the diagnosis or clinical course of patients with acute abdominal conditions.
- The concurrent use of anticholinergics with HYCODAN may produce paralytic ileus [see Drug Interactions (7.9)].
- The hydrocodone in HYCODAN may result in constipation or obstructive bowel disease, especially in patients with underlying intestinal motility disorders. Use with caution in patients with underlying intestinal motility disorders.
- The hydrocodone in HYCODAN may cause spasm of the sphincter of Oddi, resulting in an increase in biliary tract pressure. Opioids may cause increases in serum amylase [see Warnings and Precautions (5.15)]. Monitor patients with biliary tract disease, including acute pancreatitis for worsening symptoms.

5.10 Risks of Use in Patients with Head Injury, Impaired Consciousness, Increased Intracranial Pressure, or Brain Tumors

Avoid the use of HYCODAN in patients with head injury, intracranial lesions, or a pre-existing increase in intracranial pressure. In patients who may be susceptible to the intracranial effects of CO2 retention (e.g., those with evidence of increased intracranial pressure or brain tumors), HYCODAN may reduce respiratory drive, and the resultant CO2 retention can further increase intracranial pressure. Furthermore, opioids produce adverse reactions that may obscure the clinical course of patients with head injuries.

5.11 Increased Risk of Seizures in Patients with Seizure Disorders

The hydrocodone in HYCODAN may increase the frequency of seizures in patients with seizure disorders, and may increase the risk of seizures occurring in other clinical settings associated with seizures. Monitor patients with a history of seizure disorders for worsened seizure control during HYCODAN therapy.

5.12 Severe Hypotension

HYCODAN may cause severe hypotension including orthostatic hypotension and syncope in ambulatory patients. There is increased risk in patients whose ability to maintain blood pressure has already been compromised by a reduced blood volume or concurrent administration of certain CNS depressant drugs (e.g., phenothiazines or general anesthetics) [see Drug Interactions (7.4)]. Monitor these patients for signs of hypotension after initiating HYCODAN.

In patients with circulatory shock, HYCODAN may cause vasodilation that can further reduce cardiac output and blood pressure. Avoid the use of HYCODAN in patients with circulatory shock.

5.13 Neonatal Opioid Withdrawal Syndrome

HYCODAN is not recommended for use in pregnant women. Prolonged use of HYCODAN during pregnancy can result in withdrawal in the neonate. Neonatal opioid withdrawal syndrome, unlike opioid withdrawal syndrome in adults, may be life-threatening if not recognized and treated, and requires management according to protocols developed by neonatology experts. Observe newborns for signs of neonatal opioid withdrawal syndrome and manage accordingly. Advise pregnant women using opioids for a prolonged period of the risk of neonatal opioid withdrawal syndrome and ensure that appropriate treatment will be available [see Use in Specific Populations (8.1), Patient Counseling Information (17)].

5.14 Adrenal Insufficiency

Cases of adrenal insufficiency have been reported with opioid use, more often following greater than one month of use. Presentation of adrenal insufficiency may include non-specific symptoms and signs including nausea, vomiting, anorexia, fatigue, weakness, dizziness, and low blood pressure. If adrenal insufficiency is suspected, confirm the diagnosis with diagnostic testing as soon as possible. If adrenal insufficiency is diagnosed, treat with physiologic replacement doses of corticosteroids. Wean the patient off of the opioid to allow adrenal function to recover and continue corticosteroid treatment until adrenal function recovers. Other opioids may be tried as some cases reported use of a different opioid without recurrence of adrenal insufficiency. The information available does not identify any particular opioids as being more likely to be associated with adrenal insufficiency.

5.15 Drug/Laboratory Test Interactions

Because opioid agonists may increase biliary tract pressure, with resultant increase in plasma amylase or lipase levels, determination of these enzyme levels may be unreliable for 24 hours after administration of a dose of HYCODAN.

6 ADVERSE REACTIONS

The following clinically significant adverse reactions are described elsewhere in labeling:

- Addiction, abuse, and misuse [see Warnings and Precautions (5.1), Drug Abuse and Dependence (9.3)]
- Life-threatening respiratory depression [see Warnings and Precautions (5.2, 5.3, 5.4, 5.8), Overdosage (10)]
- Accidental overdose and death due to medication errors [see Warnings and Precautions (5.5)]
- Decreased mental alertness with impaired mental and/or physical abilities [see Warnings and Precautions (5.6)]
- Interactions with benzodiazepines and other CNS depressants [see Warnings and Precautions (5.8), Drug Interactions (7.1, 7.4)]
- Paralytic ileus, gastrointestinal adverse reactions [see Warnings and Precautions (5.9)]
- Increased intracranial pressure [see Warnings and Precautions (5.10)]
- Obscured clinical course in patients with head injuries [see Warnings and Precautions (5.10)]
- Seizures [see Warnings and Precautions (5.11)]
- Severe hypotension [see Warnings and Precautions (5.12)]
- Neonatal Opioid Withdrawal Syndrome [see Warnings and Precautions (5.13)]
- Adrenal insufficiency [see Warnings and Precautions (5.14)]

The following adverse reactions have been identified during clinical studies, in the literature, or during post-approval use of hydrocodone and/or homatropine. Because these reactions may be reported voluntarily from a population of uncertain size, it is not always possible to reliably estimate their frequency or establish a causal relationship to drug exposure.

The most common adverse reactions to HYCODAN include: Sedation (somnolence, mental clouding, lethargy), impaired mental and physical performance, lightheadedness, dizziness, headache, dry mouth, nausea, vomiting, and constipation.

Other reactions include:

Anaphylaxis: Anaphylaxis has been reported with hydrocodone, one of the ingredients in HYCODAN.

Body as a whole: Coma, death, fatigue, falling injuries, lethargy.

Cardiovascular: Peripheral edema, increased blood pressure, decreased blood pressure, tachycardia, chest pain, palpitation, syncope, orthostatic hypotension, prolonged QT interval, hot flush.

Central Nervous System: Facial dyskinesia, insomnia, migraine, increased intracranial pressure, seizure, tremor.

Dermatologic: Flushing, hyperhidrosis, pruritus, rash.

Endocrine/Metabolic: Cases of serotonin syndrome, a potentially life-threatening condition, have been reported during concomitant use of opioids with serotonergic drugs. Cases of adrenal insufficiency have been reported with opioid use, more often following greater than one month of use. Cases of androgen deficiency have occurred with chronic use of opioids.

Gastrointestinal: Abdominal pain, bowel obstruction, decreased appetite, diarrhea, difficulty swallowing, dry mouth, GERD, indigestion, pancreatitis, paralytic ileus, biliary tract spasm (spasm of the sphincter of Oddi).

Genitourinary: Urinary tract infection, ureteral spasm, spasm of vesicle sphincters, urinary retention.

Laboratory: Increases in serum amylase.

Musculoskeletal: Arthralgia, backache, muscle spasm.

Ophthalmic: Miosis (constricted pupils), visual disturbances.

Psychiatric: Agitation, anxiety, confusion, fear, dysphoria, depression.

Reproductive: Hypogonadism, infertility.

Respiratory: Bronchitis, cough, dyspnea, nasal congestion, nasopharyngitis, respiratory depression, sinusitis, upper respiratory tract infection.

Other: Drug abuse, drug dependence, opioid withdrawal syndrome.

Hypoglycemia: Cases of hypoglycemia have been reported in patients taking opioids. Most reports were in patients with at least one predisposing risk factor (e.g., diabetes).

7 DRUG INTERACTIONS

No specific drug interaction studies have been conducted with HYCODAN.

7.1 Alcohol

Concomitant use of alcohol with HYCODAN can result in an increase of hydrocodone plasma levels and potentially fatal overdose of hydrocodone. Instruct patients not to consume alcoholic beverages or use prescription or nonprescription products containing alcohol while on HYCODAN therapy [see Warnings and Precautions (5.8), Clinical Pharmacology (12.3)].

7.2 Inhibitors of CYP3A4 and CYP2D6

The concomitant use of HYCODAN and CYP3A4 inhibitors, such as macrolide antibiotics (e.g., erythromycin), azole-antifungal agents (e.g., ketoconazole), or protease inhibitors (e.g., ritonavir), can increase the plasma concentration of hydrocodone, resulting in increased or prolonged opioid effects. These effects could be more pronounced with concomitant use of HYCODAN and CYP2D6 and CYP3A4 inhibitors, particularly when an inhibitor is added after a stable dose of HYCODAN is achieved [see Warnings and Precautions (5.7)]. After stopping a CYP3A4 inhibitor, as the effects of the inhibitor decline, the hydrocodone plasma concentration will decrease [see Clinical Pharmacology (12.3)], resulting in decreased opioid efficacy or a withdrawal syndrome in patients who had developed physical dependence to hydrocodone.

Avoid the use of HYCODAN while taking a CYP3A4 or CYP2D6 inhibitor. If concomitant use is necessary, monitor patients for respiratory depression and sedation at frequent intervals.

7.3 CYP3A4 Inducers

The concomitant use of HYCODAN and CYP3A4 inducers such as rifampin, carbamazepine, or phenytoin, can decrease the plasma concentration of hydrocodone [see Clinical Pharmacology (12.3)], resulting in decreased efficacy or onset of a withdrawal syndrome in patients who have developed physical dependence to hydrocodone [see Warnings and Precautions (5.7)]. After stopping a CYP3A4 inducer, as the effects of the inducer decline, the hydrocodone plasma concentration will increase [see Clinical Pharmacology (12.3)], which could increase or prolong both the therapeutic effects and adverse reactions, and may cause serious respiratory depression.

Avoid the use of HYCODAN in patients who are taking CYP3A4 inducers. If concomitant use of a CYP3A4 inducer is necessary, follow the patient for reduced efficacy.

7.4 Benzodiazepines, and Other CNS Depressants

Due to additive pharmacologic effect, the concomitant use of benzodiazepines or other CNS depressants, including alcohol, other sedatives/hypnotics, anxiolytics, tranquilizers, muscle relaxants, general anesthetics, antipsychotics, and other opioids, can increase the risk of hypotension, respiratory depression, profound sedation, coma, and death. Avoid the use of HYCODAN in patients who are taking benzodiazepines or other CNS depressants [see Warnings and Precautions (5.8)], and instruct patients to avoid consumption of alcohol while on HYCODAN [see Drug Interactions (7.1), Patient Counseling Information (17)].

7.5 Serotonergic Drugs

The concomitant use of opioids with other drugs that affect the serotonergic neurotransmitter system has resulted in serotonin syndrome. If concomitant use is warranted, carefully observe the patient, particularly during treatment initiation. Discontinue HYCODAN if serotonin syndrome is suspected.

7.6 Monoamine Oxidase Inhibitors (MAOIs)

Avoid the use of HYCODAN in patients who are taking monoamine oxidase inhibitors (MAOIs) or have taken MAOIs within 14 days. The use of MAOIs or tricyclic antidepressants with hydrocodone, one of the active ingredients in HYCODAN, may increase the effect of either the antidepressant or hydrocodone. MAOI interactions with opioids may manifest as serotonin syndrome or opioid toxicity (e.g., respiratory depression, coma).

7.7 Muscle Relaxants

Hydrocodone may enhance the neuromuscular blocking action of skeletal muscle relaxants and produce an increased degree of respiratory depression. Avoid the use of HYCODAN in patients taking muscle relaxants. If concomitant use is necessary, monitor patients for signs of respiratory depression that may be greater than otherwise expected.

7.8 Diuretics

Opioids can reduce the efficacy of diuretics by inducing the release of antidiuretic hormone. Monitor patients for signs of diminished diuresis and/or effects on blood pressure and increase the dosage of the diuretic as needed.

7.9 Anticholinergic Drugs

The concomitant use of anticholinergic drugs with HYCODAN may increase risk of urinary retention and/or severe constipation, which may lead to paralytic ileus [see Warnings and Precautions (5.9)]. Monitor patients for signs of urinary retention or reduced gastric motility when HYCODAN is used concomitantly with anticholinergic drugs.

8 USE IN SPECIFIC POPULATIONS

8.1 Pregnancy

Risk Summary

HYCODAN is not recommended for use in pregnant women, including during or immediately prior to labor.

Prolonged use of opioids during pregnancy may cause neonatal opioid withdrawal syndrome [see Warnings and Precautions (5.13), Clinical Considerations].

There are no available data with HYCODAN use in pregnant women to inform a drug-associated risk for adverse developmental outcomes. Published studies with hydrocodone have reported inconsistent findings and have important methodological limitations (see Data).

Reproductive toxicity studies have not been conducted with HYCODAN; however, studies are available with individual active ingredients or related active ingredients (see Data).

In animal reproduction studies, hydrocodone administered by the subcutaneous route to pregnant hamsters during the period of organogenesis produced a teratogenic effect at a dose approximately 45 times the maximum recommended human dose (MRHD) (see Data).

Based on the animal data, advise pregnant women of the potential risk to a fetus.

The estimated background risk of major birth defects and miscarriage for the indicated population is unknown. All pregnancies have a background risk of birth defect, loss, or other adverse outcomes. In the U.S. general population, the estimated background risk of major birth defects and miscarriage in clinically recognized pregnancies is 2 to 4% and 15 to 20%, respectively.

Clinical Considerations

Fetal/Neonatal Adverse Reactions

Prolonged use of opioid analgesics during pregnancy for medical or nonmedical purposes can result in physical dependence in the neonate and neonatal opioid withdrawal syndrome shortly after birth.

Neonatal opioid withdrawal syndrome presents as irritability, hyperactivity and abnormal sleep pattern, high pitched cry, tremor, vomiting, diarrhea and failure to gain weight. The onset, duration, and severity of neonatal opioid withdrawal syndrome vary based on the specific opioid used, duration of use, timing and amount of last maternal use, and rate of elimination of the drug by the newborn. Observe newborns for symptoms of neonatal opioid withdrawal syndrome and manage accordingly [see Warnings and Precautions (5.13)].

Labor or Delivery

Opioids cross the placenta and may produce respiratory depression and psycho-physiologic effects in neonates. An opioid antagonist, such as naloxone, must be available for reversal of opioid-induced respiratory depression in the neonate. Opioids, including HYCODAN, can prolong labor through actions which temporarily reduce the strength, duration, and frequency of uterine contractions. However, this effect is not consistent and may be offset by an increased rate of cervical dilation, which tends to shorten labor. Monitor neonates exposed to opioids during labor for signs of excess sedation and respiratory depression.

Data

Human Data

Hydrocodone

A limited number of pregnancies have been reported in published observational studies and postmarketing reports describing hydrocodone use during pregnancy. However, these data cannot definitely establish or exclude any drug-associated risk during pregnancy. Methodological limitations of these observational studies include small sample size and lack of details regarding dose, duration and timing of exposure.

Animal Data

Reproductive toxicity studies have not been conducted with HYCODAN; however, studies are available with individual active ingredients or related active ingredients.

Hydrocodone

In an embryofetal development study in pregnant hamsters dosed on gestation day 8 during the period of organogenesis, hydrocodone induced cranioschisis, a malformation, at approximately 45 times the MRHD (on a mg/m^2 basis with a maternal subcutaneous dose of 102 mg/kg). Reproductive toxicology studies were also conducted with codeine, an opiate related to hydrocodone. In an embryofetal development study in pregnant rats dosed throughout the period of organogenesis, codeine increased resorptions and decreased fetal weights at a dose approximately 65 times the MRHD of hydrocodone (on a mg/m^2 basis with a maternal oral dose of codeine at 120 mg/kg/day); however, these effects occurred in the presence of maternal toxicity. In embryofetal development studies with pregnant rabbits and mice dosed throughout the period of organogenesis, codeine produced no adverse developmental effects at doses approximately 30 and 160 times, respectively, the MRHD of hydrocodone (on a mg/m^2 basis with maternal oral doses of codeine at 30 mg/kg/day in rabbits and 600 mg/kg/day in mice).

Homatropine

Animal studies with homatropine are not available.

8.2 Lactation

Risk Summary

Because of the potential for serious adverse reactions, including excess sedation, respiratory depression, and death in a breastfed infant, advise patients that breastfeeding is not recommended during treatment with HYCODAN.

There are no data on the presence of HYCODAN in human milk, the effects of HYCODAN on the breastfed infant, or the effects of HYCODAN on milk production; however, data are available with hydrocodone and homatropine.

Hydrocodone

Hydrocodone is present in breast milk. Published cases report variable concentrations of hydrocodone and hydromorphone (an active metabolite) in breast milk with administration of immediate-release hydrocodone to nursing mothers in the early post-partum period with relative infant doses of hydrocodone ranging between 1.4% and 3.7%. There are case reports of excessive sedation and respiratory depression in breastfed infants exposed to hydrocodone. No information is available on the effects of hydrocodone on milk production.

Homatropine

No information is available on the levels of homatropine in breast milk or on milk production. The published literature suggests that homatropine may decrease milk production based on its anticholinergic effects (see Clinical Considerations).

Clinical Considerations

Infants exposed to HYCODAN through breast milk should be monitored for excess sedation and respiratory depression. Withdrawal symptoms can occur in breastfed infants when maternal administration of an opioid is stopped, or when breastfeeding is stopped.

8.3 Females and Males of Reproductive Potential

Infertility

Chronic use of opioids, such as hydrocodone, a component of HYCODAN, may cause reduced fertility in females and males of reproductive potential. It is not known whether these effects on fertility are reversible [see Adverse Reactions (6), Clinical Pharmacology (12.2)].

8.4 Pediatric Use

HYCODAN is contraindicated in pediatric patients younger than 6 years of age because of life-threatening respiratory depression and death have occurred in pediatric patients who received hydrocodone [see Contraindications (4), Warnings and Precautions (5.2)].

The safety and effectiveness of HYCODAN have not been established in patients younger than 18 years of age. HYCODAN is not recommended for use in patients younger than 18 years of age because the benefits of symptomatic treatment of cough associated with allergies or the common cold do not outweigh the risks for use of hydrocodone in these patients [see Indications (1), Warnings and Precautions (5.3)].

8.5 Geriatric Use

Clinical studies have not been conducted with HYCODAN in geriatric populations.

Use caution when considering the use of HYCODAN in patients 65 years of age or older. Elderly patients may have increased sensitivity to hydrocodone; greater frequency of decreased hepatic, renal, or cardiac function; or concomitant disease or other drug therapy [see Warnings and Precautions (5.4)].

Respiratory depression is the chief risk for elderly patients treated with opioids, including HYCODAN. Respiratory depression has occurred after large initial doses of opioids were administered to patients who were not opioid-tolerant or when opioids were co-administered with other agents that depress respiration [see Warnings and Precautions (5.4, 5.8)].

Hydrocodone is known to be substantially excreted by the kidney, and the risk of adverse reactions to this drug may be greater in patients with impaired renal function. Because elderly patients are more likely to have decreased renal function, monitor these patients closely for respiratory depression, sedation, and hypotension.

8.6 Renal Impairment

The pharmacokinetics of HYCODAN has not been characterized in patients with renal impairment. Patients with renal impairment may have higher plasma concentrations than those with normal function [see Clinical Pharmacology (12.3)]. HYCODAN should be used with caution in patients with severe impairment of renal function, and patients should be monitored closely for respiratory depression, sedation, and hypotension.

8.7 Hepatic Impairment

The pharmacokinetics of HYCODAN has not been characterized in patients with hepatic impairment. Patients with severe hepatic impairment may have higher plasma concentrations than those with normal hepatic function [see Clinical Pharmacology (12.3)]. Therefore, HYCODAN should be used with caution in patients with severe impairment of hepatic function, and patients should be monitored closely for respiratory depression, sedation, and hypotension.

9 DRUG ABUSE AND DEPENDENCE

9.1 Controlled Substance

HYCODAN contains hydrocodone, a Schedule II controlled substance.

9.2 Abuse

Hydrocodone

HYCODAN contains hydrocodone, a substance with a high potential for abuse similar to other opioids including morphine and codeine. HYCODAN can be abused and is subject to misuse, addiction, and criminal diversion [see Warnings and Precautions (5.1)].

All patients treated with opioids require careful monitoring for signs of abuse and addiction, since use of opioid analgesic and antitussive products carries the risk of addiction even under appropriate medical use.

Prescription drug abuse is the intentional non-therapeutic use of a prescription drug, even once, for its rewarding psychological or physiological effects.

Drug addiction is a cluster of behavioral, cognitive, and physiological phenomena that develop after repeated substance use and includes: a strong desire to take the drug, difficulties in controlling its use, persisting in its use despite harmful consequences, a higher priority given to drug use than to other activities and obligations, increased tolerance, and sometimes a physical withdrawal.

"Drug-seeking" behavior is very common in persons with substance use disorders. Drug-seeking tactics include emergency calls or visits near the end of office hours, refusal to undergo appropriate examination, testing, or referral, repeated "loss" of prescriptions, tampering with prescriptions, and reluctance to provide prior medical records or contact information for other treating health care provider(s). "Doctor shopping" (visiting multiple prescribers to obtain additional prescriptions) is common among drug abusers and people suffering from untreated addiction. Preoccupation with achieving adequate pain relief can be appropriate behavior in a patient with poor pain control.

Abuse and addiction are separate and distinct from physical dependence and tolerance. Health care providers should be aware that addiction may not be accompanied by concurrent tolerance and symptoms of physical dependence in all addicts. In addition, abuse of opioids can occur in the absence of true addiction.

HYCODAN, like other opioids, can be diverted for non-medical use into illicit channels of distribution. Careful record-keeping of prescribing information, including quantity, frequency, and renewal requests, as required by state and federal law, is strongly advised.

Proper assessment of the patient, proper prescribing practices, periodic re-evaluation of therapy, and proper dispensing and storage are appropriate measures that help to limit abuse of opioid drugs.

Risks Specific to Abuse of HYCODAN

HYCODAN is for oral use only. Abuse of HYCODAN poses a risk of overdose and death. The risk is increased with concurrent use of HYCODAN with alcohol and other central nervous system depressants [see Warnings and Precautions (5.8), Drug Interactions (7.1, 7.4)].

Parenteral drug abuse is commonly associated with transmission of infectious diseases such as hepatitis and HIV.

9.3 Dependence

Psychological dependence, physical dependence, and tolerance may develop upon repeated administration of opioids; therefore, HYCODAN should be prescribed and administered for the shortest duration that is consistent with individual patient treatment goals and patients should be reevaluated prior to refills [see Dosage and Administration (2.3), Warnings and Precautions (5.1)].

Physical dependence, the condition in which continued administration of the drug is required to prevent the appearance of a withdrawal syndrome, assumes clinically significant proportions only after several weeks of continued oral opioid use, although some mild degree of physical dependence may develop after a few days of opioid therapy.

If HYCODAN is abruptly discontinued in a physically-dependent patient, a withdrawal syndrome may occur. Withdrawal also may be precipitated through the administration of drugs with opioid antagonist activity (e.g., naloxone, nalmefene), mixed agonist/antagonist analgesics (e.g., pentazocine, butorphanol, nalbuphine), or partial agonists (e.g., buprenorphine). Some or all of the following can characterize this syndrome: restlessness, lacrimation, rhinorrhea, yawning, perspiration, chills, myalgia, and mydriasis. Other signs and symptoms also may develop, including irritability, anxiety, backache, joint pain, weakness, abdominal cramps, insomnia, nausea, anorexia, vomiting, diarrhea, or increased blood pressure, respiratory rate, or heart rate.

Infants born to mothers physically dependent on opioids will also be physically dependent and may exhibit respiratory difficulties and withdrawal signs [see Use in Specific Populations (8.1)].

10 OVERDOSAGE

Clinical Presentation

Hydrocodone

Acute overdose with hydrocodone is characterized by respiratory depression (a decrease in respiratory rate and/or tidal volume, Cheyne-Stokes respiration, cyanosis), extreme somnolence progressing to stupor or coma, skeletal muscle flaccidity, cold and clammy skin, constricted pupils, and, in some cases, pulmonary edema, bradycardia, partial or complete airway obstruction, atypical snoring, hypotension, hypoglycemia, circulatory collapse, cardiac arrest, and death.

Hydrocodone may cause miosis, even in total darkness. Pinpoint pupils are a sign of opioid overdose but are not pathognomonic (e.g., pontine lesions of hemorrhagic or ischemic origin may produce similar findings). Marked mydriasis rather than miosis may be seen with hypoxia in overdose situations [see Clinical Pharmacology (12.2)].

Homatropine

Homatropine has broad, nonspecific anticholinergic / antimuscarinic activity that similar to, although less potent than, atropine. Overdosage of homatropine can cause mydriasis and cycloplegia (fixed and dilated pupils), dry mouth and eyes, decreased sweating, hyperthermia, flushing, headache, visual blurring, gastrointestinal symptoms, constipation, urinary retention, tachycardia and palpitations, anxiety, restlessness, agitation, hallucinations, convulsions, cardiac arrhythmias and coma. Anticholinergic agents can also precipitate acute narrow angle glaucoma.

Treatment of Overdose

Treatment of overdosage is driven by the overall clinical presentation, and consists of discontinuation of HYCODAN together with institution of appropriate therapy. Give primary attention to the reestablishment of adequate respiratory exchange through provision of a patent and protected airway and the institution of assisted or controlled ventilation. Employ other supportive measures (including oxygen and vasopressors) in the management of circulatory shock and pulmonary edema as indicated. Cardiac arrest or arrhythmias will require advanced life-support techniques. Gastric emptying may be useful in removing unabsorbed drug.

The opioid antagonists, naloxone and nalmefene, are specific antidotes for respiratory depression resulting from opioid overdose. For clinically significant respiratory or circulatory depression secondary to hydrocodone overdose, administer an opioid antagonist. An antagonist should not be administered in the absence of clinically significant respiratory depression. Because the duration of opioid reversal is expected to be less than the duration of action of hydrocodone in HYCODAN, carefully monitor the patient until spontaneous respiration is reliably reestablished. If the response to an opioid antagonist is suboptimal or only brief in nature, administer additional antagonist as directed by the product's prescribing information.

Hemodialysis is not routinely used to enhance the elimination of hydrocodone from the body.

Physostigmine may be used parenterally for the treatment of the signs and symptoms of homatropine toxicity.

11 DESCRIPTION

HYCODAN tablets and oral solution contain hydrocodone, an opioid agonist; and homatropine, a muscarinic antagonist.

Each tablet or spoonful (5 mL) of HYCODAN contains 5 mg of hydrocodone bitartrate, USP and 1.5 mg of homatropine methylbromide, USP, for oral administration.

HYCODAN tablets also contain: calcium phosphate dibasic, colloidal silicon dioxide, lactose, magnesium stearate, pregelatinized starch and stearic acid.

HYCODAN oral solution also contains: anhydrous citric acid, FD&C Red 40, methylparaben, natural and artificial cherry flavor, propylparaben, purified water, sorbitol solution, sodium citrate dihydrate and sucrose.

Hydrocodone Bitartrate

The chemical name for hydrocodone bitartrate is morphinan-6-one, 4,5-epoxy-3-methoxy-17-methyl-, (5α)-, [R-(R*,R*)]-2,3-dihydroxybutanedioate (1:1), hydrate (2:5). It is also known as 4,5α-Epoxy-3-methoxy-17-methylmorphinan-6-one tartrate (1:1) hydrate (2:5). It occurs as a fine white crystal or crystalline powder, which is derived from the opium alkaloid, thebaine. It has a molecular weight of 494.50 and has the following chemical structure:

C18H21NO3 ∙ C4H6O6 ∙ 2½H2O MW 494.490

Homatropine Methylbromide

The chemical name for homatropine methylbromide is 8-Azoniabicyclo [3.2.1]octane,3-[(hydroxyphenyl-acetyl)oxy]-8,8-dimethyl-,bromide, endo-. It occurs as a white crystal or fine white crystalline powder. It has a molecular weight of 370.29 and has the following chemical structure:

C17H24BrNO3
HOMATROPINE METHYLBROMIDE

12 CLINICAL PHARMACOLOGY

12.1 Mechanism of Action

Hydrocodone

Hydrocodone is an opioid agonist with relative selectivity for the mu-opioid receptor, although it can interact with other opioid receptors at higher doses. The precise mechanism of action of hydrocodone and other opiates is not known; however, hydrocodone is believed to act centrally on the cough center. In excessive doses, hydrocodone will depress respiration.

Homatropine

Homatropine is an anticholinergic that inhibits activity of the muscarinic acetylcholine receptor with less potency than atropine.

12.2 Pharmacodynamics

Hydrocodone

Effects on the Central Nervous System

Hydrocodone produces respiratory depression by direct action on brain stem respiratory centers. The respiratory depression involves a reduction in the responsiveness of the brain stem respiratory centers to both increases in carbon dioxide tension and to electrical stimulation.

Hydrocodone causes miosis, even in total darkness. Pinpoint pupils are a sign of opioid overdose but are not pathognomonic (e.g., pontine lesions of hemorrhagic or ischemic origins may produce similar findings). Marked mydriasis rather than miosis may be seen due to hypoxia in overdose situations.

Effects on the Gastrointestinal Tract and Other Smooth Muscle

Hydrocodone causes a reduction in motility associated with an increase in smooth muscle tone in the antrum of the stomach and duodenum. Digestion of food in the small intestine is delayed and propulsive contractions are decreased. Propulsive peristaltic waves in the colon are decreased, while tone may be increased to the point of spasm resulting in constipation. Other opioid-induced effects may include a reduction in biliary and pancreatic secretions, spasm of sphincter of Oddi, and transient elevations in serum amylase.

Effects on the Cardiovascular System

Hydrocodone produces peripheral vasodilation which may result in orthostatic hypotension or syncope. Manifestations of histamine release and/or peripheral vasodilation may include pruritus, flushing, red eyes and sweating and/or orthostatic hypotension.

Effects on the Endocrine System

Opioids inhibit the secretion of adrenocorticotropic hormone (ACTH), cortisol, and luteinizing hormone (LH) in humans [see Adverse Reactions (6)]. They also stimulate prolactin, growth hormone (GH) secretion, and pancreatic secretion of insulin and glucagon.

Chronic use of opioids may influence the hypothalamic-pituitary-gonadal axis, leading to androgen deficiency that may manifest as low libido, impotence, erectile dysfunction, amenorrhea, or infertility. The causal role of opioids in the clinical syndrome of hypogonadism is unknown because the various medical, physical, lifestyle, and psychological stressors that may influence gonadal hormone levels have not been adequately controlled for in studies conducted to date [see Adverse Reactions (6)].

Effects on the Immune System

Opioids have been shown to have a variety of effects on components of the immune system in in vitro and animal models. The clinical significance of these findings is unknown. Overall, the effects of opioids appear to be modestly immunosuppressive.

Concentration–Adverse Reaction Relationships

There is a relationship between increasing hydrocodone plasma concentration and increasing frequency of dose-related opioid adverse reactions such as nausea, vomiting, CNS effects, and respiratory depression. In opioid-tolerant patients, the situation may be altered by the development of tolerance to opioid-related adverse reactions.

Homatropine

Homatropine methylbromide has several mild but undesirable clinical properties resulting from its antisecretory effects. These can include: dry mouth, loss of visual accommodation, photophobia, and difficulty in urination. The extent of the above actions is dictated by dose, dose escalation, therefore, results in progressively aversive symptoms in patients.

12.3 Pharmacokinetics

Absorption

Following a 10 mg oral dose of hydrocodone administered to five adult male subjects, the mean peak concentration was 23.6 ± 5.2 ng/mL. Maximum serum levels were achieved at 1.3 ± 0.3 hours. Food has no significant effect on the extent of absorption of hydrocodone.

Distribution

Although the extent of protein binding of hydrocodone in human plasma has not been definitively determined, structural similarities to related opioid analgesics suggest that hydrocodone is not extensively protein bound. As most agents in the 5-ring morphinan group of semi-synthetic opioids bind plasma protein to a similar degree (range 19% [hydromorphone] to 45% [oxycodone]), hydrocodone is expected to fall within this range.

Elimination

Metabolism

Hydrocodone exhibits a complex pattern of metabolism, including N-demethylation, O-demethylation, and 6keto reduction to the corresponding 6-α-and 6-β-hydroxy metabolites. CYP3A4 mediated N-demethylation to norhydrocodone is the primary metabolic pathway of hydrocodone with a lower contribution from CYP2D6-mediated O-demethylation to hydromorphone. Hydromorphone is formed from the O-demethylation of hydrocodone and may contribute to the total analgesic effect of hydrocodone. Therefore, the formation of these and related metabolites can, in theory, be affected by other drugs [see Drug Interactions (7.2)]. Published in vitro studies have shown that N-demethylation of hydrocodone to form norhydrocodone can be attributed to CYP3A4 while O-demethylation of hydrocodone to hydromorphone is predominantly catalyzed by CYP2D6 and to a lesser extent by an unknown low affinity CYP enzyme.

Excretion

Hydrocodone and its metabolites are eliminated primarily in the kidneys. The mean plasma half-life of hydrocodone is approximately 4 hours.

13 NONCLINICAL TOXICOLOGY

13.1 Carcinogenesis, Mutagenesis, Impairment of Fertility

Carcinogenicity, mutagenicity, and fertility studies have not been conducted with HYCODAN; however, published information is available for the individual active ingredients or related active ingredients.

Hydrocodone

Carcinogenicity studies were conducted with codeine, an opiate related to hydrocodone. Two-year studies in F344/N rats and B6C3F1 mice were conducted to assess the carcinogenic potential of codeine. No evidence of tumorigenicity was observed in male and female rats at codeine dietary doses up to 70 and 80 mg/kg/day (approximately equivalent to 40 and 45 times the MRHD of hydrocodone on a mg/m^2 basis, respectively). No evidence of tumorigenicity was observed in male and female mice at codeine dietary doses up to 400 mg/kg/day (approximately equivalent to 110 times the MRHD of hydrocodone on a mg/m^2 basis).

Mutagenicity studies with hydrocodone have not been conducted.

Fertility studies with hydrocodone have not been conducted.

Homatropine

Carcinogenicity, mutagenicity, and fertility studies with homatropine have not been conducted.

16 HOW SUPPLIED/STORAGE AND HANDLING

HYCODAN is supplied as a white-colored, biconvex tablet, one face bisected and debossed with "205", and the other face plain, available in:

 | NDC 64950-205-03 | Bottles of 30
 | NDC 64950-205-10 | Bottles of 100

Store tablets at controlled room temperature 20°C to 25°C (68°F to 77°F) [See USP Controlled Room Temperature]. Dispense in a tight, light–resistant container, as defined in the USP, with a child-resistant closure.

HYCODAN is available as a clear red-colored, cherry-flavored oral solution in:

NDC 64950-342-05: Unit Dose Cup of 5 mL
NDC 64950-342-45: Case contains 40 unit dose cups of 5 mL (NDC 64950-342-05), packaged in 4 trays of 10 unit dose cups each
NDC 64950-342-47: Bottle of 473 mL

STORAGE AND HANDLING

Store oral solution at controlled room temperature 20°C to 25°C (68°F to 77°F). [See USP Controlled Room Temperature.]

Dispense in a tight, light-resistant container, as defined in the USP, with a child-resistant closure.

Ensure that patients have an oral dosing dispenser that measures the appropriate volume in milliliters. Counsel patients on how to utilize an oral dosing dispenser and correctly measure the oral suspension as prescribed.

17 PATIENT COUNSELING INFORMATION

Advise the patient to read the FDA-approved patient labeling (Medication Guide).

Addiction, Abuse, and Misuse

Inform patients that the use of HYCODAN, even when taken as recommended, can result in addiction, abuse, and misuse, which can lead to overdose and death [see Warnings and Precautions (5.1)]. Instruct patients not to share HYCODAN with others and to take steps to protect HYCODAN from theft or misuse.

Important Dosing and Administration Instructions

Instruct patients how to measure and take the correct dose of HYCODAN. Advise patients to measure HYCODAN with an accurate milliliter measuring device. Patients should be informed that a household teaspoon is not an accurate measuring device and could lead to overdosage. Advise patients to ask their pharmacist to recommend an appropriate measuring device and for instructions for measuring the correct dose [see Dosage and Administration (2.1), Warnings and Precautions (5.5)]. Advise patients not to increase the dose or dosing frequency of HYCODAN because serious adverse events such as respiratory depression may occur with overdosage [see Warnings and Precautions (5.2), Overdosage (10)].

Life-Threatening Respiratory Depression

Inform patients of the risk of life-threatening respiratory depression, including information that the risk is greatest when starting HYCODAN and that it can occur even at recommended dosages [see Warnings and Precautions (5.2)]. Advise patients how to recognize respiratory depression and to seek medical attention if breathing difficulties develop.

Accidental Ingestion

Inform patients that accidental ingestion, especially by children, may result in respiratory depression or death [see Warnings and Precautions (5.2)]. Instruct patients to take steps to store HYCODAN securely and to properly dispose of unused HYCODAN in accordance with the local state guidelines and/or regulations.

Activities Requiring Mental Alertness

Advise patients to avoid engaging in hazardous tasks that require mental alertness and motor coordination such as operating machinery or driving a motor vehicle as HYCODAN may produce marked drowsiness [see Warnings and Precautions (5.6)].

Interactions with Benzodiazepines and Other Central Nervous System Depressants, Including Alcohol

Inform patients and caregivers that potentially fatal additive effects may occur if HYCODAN is used with benzodiazepines or other CNS depressants, including alcohol. Advise patients to avoid concomitant use of HYCODAN with benzodiazepines or other CNS depressants and instruct patients not to consume alcoholic beverages, as well as prescription and over-the-counter products that contain alcohol, during treatment with HYCODAN [see Warnings and Precautions (5.8), Drug Interactions (7.1, 7.4)].

Constipation

Advise patients of the potential for severe constipation [see Warnings and Precautions (5.9), Adverse Reactions (6)].

Anaphylaxis

Inform patients that anaphylaxis has been reported with ingredients contained in HYCODAN. Advise patients how to recognize such a reaction and when to seek medical attention [see Contraindications (4), Adverse Reactions (6)].

MAOI Interaction

Inform patients not to take HYCODAN while using or within 14 days of stopping any drugs that inhibit monoamine oxidase. Patients should not start MAOIs while taking HYCODAN [see Drug Interactions (7.6)].

Hypotension

Inform patients that HYCODAN may cause orthostatic hypotension and syncope. Instruct patients how to recognize symptoms of low blood pressure and how to reduce the risk of serious consequences should hypotension occur (e.g., sit or lie down, carefully rise from a sitting or lying position) [see Warnings and Precautions (5.12)].

Pregnancy

Advise patients that use of HYCODAN is not recommended during pregnancy [see Use in Specific Populations (8.1)].

Neonatal Opioid Withdrawal Syndrome

Inform female patients of reproductive potential that use of HYCODAN during pregnancy can result in neonatal opioid withdrawal syndrome, which may be life-threatening if not recognized and treated [see Warnings and Precautions (5.13), Use in Specific Populations (8.1)].

Embryo-Fetal Toxicity

Inform female patients of reproductive potential that HYCODAN can cause fetal harm and to inform their healthcare provider of a known or suspected pregnancy [see Use in Specific Populations (8.1)].

Lactation

Advise women that breastfeeding is not recommended during treatment with HYCODAN [see Use in Specific Populations (8.2)].

Infertility

Inform patients that chronic use of opioids, such as hydrocodone, a component of HYCODAN, may cause reduced fertility. It is not known whether these effects on fertility are reversible [see Use in Specific Populations (8.3)].

Adrenal Insufficiency

Inform patients that HYCODAN could cause adrenal insufficiency, a potentially life-threatening condition. Adrenal insufficiency may present with non-specific symptoms and signs such as nausea, vomiting, anorexia, fatigue, weakness, dizziness, and low blood pressure. Advise patients to seek medical attention if they experience a constellation of these symptoms [see Warnings and Precautions (5.14)].

Serotonin Syndrome

Inform patients that HYCODAN could cause a rare but potentially life-threatening condition resulting from concomitant administration of serotonergic drugs. Warn patients of the symptoms of serotonin syndrome and to seek medical attention right away if symptoms develop. Instruct patients to inform their physicians if they are taking, or plan to take serotonergic medications [see Adverse Reactions (6), Drug Interactions (7.5)].

Disposal of Unused HYCODAN

Advise patients to properly dispose of unused HYCODAN. Advise patients to throw the drug in the household trash following these steps. 1) Remove them from their original containers and mix them with an undesirable substance, such as used coffee grounds or kitty litter (this makes the drug less appealing to children and pets, and unrecognizable to people who may intentionally go through the trash seeking drugs). 2) Place the mixture in a sealable bag, empty can, or other container to prevent the drug from leaking or breaking out of a garbage bag, or to dispose of in accordance with local state guidelines and/or regulations.

Manufactured by:
Genus Lifesciences Inc.
Allentown, PA 18102

HYCODAN® is a Registered Trademark of Genus Lifesciences Inc.
© 2018 Genus Lifesciences Inc.

MEDICATION GUIDE
HYCODAN (hy-ko-dan)
(hydrocodone bitartrate and homatropine methylbromide)
tablets and oral solution, for oral use, C II

What is the most important information I should know about HYCODAN?
HYCODAN is not for children under 18 years of age.
HYCODAN can cause serious side effects, including:

- Addiction, abuse and misuse. Taking HYCODAN or other medicines that contain an opioid can cause addiction, abuse and misuse, which can lead to overdose and death. This can happen even if you take HYCODAN exactly as prescribed by your healthcare provider. Your risk of addiction, abuse, and misuse is increased if you or a family member has a history of drug or alcohol abuse or addiction, or mental health problems.
  - Do not share your HYCODAN with other people.
  - Keep HYCODAN in a safe place away from children.
- Life-threatening breathing problems (respiratory depression). HYCODAN can cause breathing problems (respiratory depression) that can happen at any time during treatment and can lead to death. Your risk of breathing problems is greatest when you first start taking HYCODAN, are taking other medicines that can cause breathing problems, have certain lung problems, are elderly, or have certain other health problems. Children are at higher risk for respiratory depression. Breathing problems can happen even if you take HYCODAN exactly as prescribed by your healthcare provider.
  Call your healthcare provider or get emergency medical help right away if anyone taking HYCODAN has any of the symptoms below:

- increased sleepiness
- confusion
- difficulty breathing

- shallow breathing
- limpness

Keep HYCODAN in a safe place away from children. Accidental use of even 1 dose of HYCODAN, especially by a child, is a medical emergency and can cause breathing problems (respiratory depression) which can lead to death. If a child accidentally takes HYCODAN, get emergency medical help right away.

- Overdose and death due to medicine dosing errors. Overdose and death can happen if you measure the wrong dose of HYCODAN. Always use an accurate milliliter (mL) measuring device to measure the correct amount of HYCODAN. Do not use a household teaspoon to measure your medicine. You may accidentally take too much. You can ask your pharmacist for the measuring device you should use and how to measure the correct dose.
- Breathing problems (respiratory depression) that can lead to death and opioid withdrawal can happen if you start taking or stop taking other medicines while taking HYCODAN, including:
  - certain antibiotics
  - certain medicines to treat a fungal infection
  - certain medicines to treat Human Immunodeficiency Virus (HIV)-1 infection, Acquired Immune Deficiency Syndrome (AIDS), or Hepatitis C
  - rifampin
  - carbamazepine
  - phenytoin
  Tell your healthcare provider if you take any of these medicines. Ask your healthcare provider or pharmacist if you are not sure if your medicine is listed above.
- Severe drowsiness, breathing problems (respiratory depression), coma, and death can happen in people who take HYCODAN with benzodiazepines or other central nervous system depressants, including alcohol.
  - Do not take benzodiazepines or any medicine that can cause drowsiness or sleepiness during treatment with HYCODAN.
  - Do not drink alcohol or take prescription or over-the-counter medicines that contain alcohol during treatment with HYCODAN.
- Opioid withdrawal in a newborn. Use of HYCODAN during pregnancy can cause withdrawal symptoms in your newborn baby that could be life-threatening if not recognized and treated. You should not take HYCODAN if you are pregnant. Tell your healthcare provider right away if you are pregnant or think you may be pregnant.

What is HYCODAN?

- HYCODAN is a prescription medicine used in adults 18 years of age and older to treat a cough. HYCODAN contains hydrocodone, an opioid (narcotic) cough suppressant.
- HYCODAN is a federal controlled substance (C-II) because it contains hydrocodone that can be abused or lead to dependence. Keep HYCODAN in a safe place to prevent misuse and abuse. Selling or giving away HYCODAN may harm others, and is against the law. Tell your healthcare provider if you have ever abused or been dependent on alcohol, prescription medicines or street drugs.

Who should not take HYCODAN?
HYCODAN is not for children under 18 years of age. See "What is the most important information I should know about HYCODAN?"
Do not take HYCODAN if you:

- have severe breathing problems (respiratory depression) or breathing problems caused by asthma. See "What is the most important information I should know about HYCODAN?"
- have a blockage (obstruction) in your bowel such as a paralytic ileus.
- are allergic to hydrocodone, homatropine, or any of the ingredients in HYCODAN. See the end of this Medication Guide for a complete list of ingredients in HYCODAN.

Ask your healthcare provider if you have any questions about this information.

Before you take HYCODAN, tell your healthcare provider about all of your medical conditions, including if you:

- have a drug addiction
- have lung or breathing problems
- have a fever and are coughing up mucus
- have had a recent head injury
- have had a brain tumor or other brain problems
- have or have had seizures
- have pain in your stomach-area (abdomen)
- have constipation or other bowel problems

- have bile duct or pancreas problems
- have glaucoma (increased pressure in eyes)
- have prostate problems
- have problems with your urinary tract or difficulty urinating
- have kidney or liver problems
- have adrenal gland problems
- have low blood pressure
- plan to have surgery

- are pregnant or plan to become pregnant. HYCODAN can harm your unborn baby. See "What is the most important information I should know about HYCODAN?"
- are breastfeeding or plan to breastfeed. Hydrocodone passes into your breast milk and can cause serious side effects in your baby including increased sleepiness, breathing problems (respiratory depression), and death. You and your healthcare provider should decide if you will take HYCODAN or breastfeed. You should not do both. See "What should I avoid while taking HYCODAN?"
- plan to have children. HYCODAN may affect the ability to have a child in females and males (fertility problems). It is not known if these fertility problems will be reversible, even after you stop taking HYCODAN. Talk to your healthcare provider if this is a concern for you.

Tell your healthcare provider about all the medicines you take, including prescription and over-the-counter medicines, vitamins, and herbal supplements.
Taking HYCODAN with certain other medicines can cause side effects or affect how well HYCODAN or the other medicines work. Do not start or stop taking other medicines without talking to your healthcare provider.
Especially tell your healthcare provider if you:

- take pain medicines such as opioids (narcotics).
- take cold or allergy medicines that contain antihistamines or cough suppressants.
- drink alcohol.
- take muscle relaxants.
- take certain medicines used to treat mood, anxiety, psychotic or thought disorders, or depression, including monoamine oxidase inhibitors (MAOIs), tricyclics, selective serotonin reuptake inhibitors (SSRIs), selective serotonin-norepinephrine reuptake inhibitors (SNRIs), or antipsychotics.
- take medicines to lower your blood pressure.
- take water pills (diuretics).
- take medicines called "anticholinergics" used to treat certain health problems including asthma, chronic obstructive pulmonary disease (COPD), or stomach problems.

Ask your healthcare provider if you are not sure if you take one of these medicines.

How should I take HYCODAN?

- See "What is the most important information I should know about HYCODAN?"
- Take HYCODAN exactly as your healthcare provider tells you to take it. Do not change your dose without talking to your healthcare provider.
- Take HYCODAN by mouth only.
- Take HYCODAN using an accurate milliliter (mL) measuring device. If you do not have one, ask your pharmacist to give you a measuring device to help you measure the correct amount of HYCODAN. Do not use a household teaspoon to measure your medicine. You may accidently take too much.
- Do not overfill the measuring device.
- Rinse the measuring device with water after each use.
- If you take too much HYCODAN, call your healthcare provider or go to the nearest hospital emergency room right away.
- Tell your healthcare provider if your cough does not get better within 5 days of treatment with HYCODAN.

What should I avoid while taking HYCODAN?

- Avoid driving a car or operating machinery during treatment with HYCODAN. HYCODAN can cause you to be drowsy, slow your thinking and motor skills, and affect your vision.
- Do not drink alcohol during treatment with HYCODAN. Drinking alcohol can increase your chances of having serious side effects.

Avoid the use of HYCODAN if you:

- are pregnant. Use of HYCODAN during pregnancy can cause withdrawal symptoms in your newborn baby that could be life-threatening if not recognized and treated. Tell your healthcare provider right away if you are pregnant or think you may be pregnant.
- are breastfeeding. Use of HYCODAN while breastfeeding can cause severe breathing problems (respiratory depression) in your breastfed infant that could be life-threatening.
- take a medicine called a monoamine oxidase inhibitor (MAOI). Avoid taking an MAOI within 14 days after you stop taking HYCODAN. Avoid starting HYCODAN if you stopped taking an MAOI in the last 14 days.

What are the possible side effects of HYCODAN?
HYCODAN can cause serious side effects, including:

- See "What is the most important information I should know about HYCODAN?"
- Bowel problems including severe constipation or stomach pain. See "Who should not take HYCODAN?"
- Increased pressure in your head (intracranial). Avoid the use of HYCODAN if you have a head injury or have been told that you have changes in the tissue of your brain (brain lesions) or increased pressure in your head.
- Increased risk of seizures in people with seizure disorders. If you have a seizure disorder, HYCODAN may increase how often you have a seizure.
- Low blood pressure. A sudden drop in blood pressure can happen in some people during treatment with HYCODAN and this may cause you to feel dizzy, faint, lightheaded, or weak, especially when you stand up (orthostatic hypotension). Your risk of having this problem may be increased if you take HYCODAN with certain other medicines that lower blood pressure. If you have any of these symptoms while taking HYCODAN, sit or lie down. Do not change your body position too fast. Get up slowly from sitting or lying down.
- Adrenal gland problems. HYCODAN can cause serious and life-threatening adrenal gland problems. Your healthcare provider may do blood tests to check for adrenal gland problems. Call your healthcare provider right away if you have any of these symptoms:

- nausea
- vomiting
- not wanting to eat (anorexia)
- fatigue

- weakness
- dizziness
- low blood pressure

The most common side effects of HYCODAN include:

- sleepiness
- confusion
- coordination problems
- decrease in mental and physical performance
- lack of energy
- lightheadedness

- dizziness
- headache
- dry mouth
- nausea
- vomiting
- constipation

These are not all the possible side effects of HYCODAN.
Call your doctor for medical advice about side effects. You may report side effects to FDA at 1-800-FDA-1088.

How should I store HYCODAN?

- Store HYCODAN at room temperature between 68°F to 77°F (20°C to 25°C).
- Store HYCODAN tablets in a tightly closed container, in a dry, cool place away from heat or direct sunlight.
- Keep HYCODAN and all medicines out of the reach of children.

How should I dispose of HYCODAN?
Remove unused HYCODAN from the container and mix it with an undesirable, non-toxic substance such as cat litter or used coffee grounds to make it less appealing to children and pets. Place the mixture in a container such as a sealed plastic bag and throw it away in the household trash. You can also follow your state or local guidelines on how to safely throw away HYCODAN.

General information about the safe and effective use of HYCODAN.
Medicines are sometimes prescribed for purposes other than those listed in a Medication Guide. Do not use HYCODAN for a condition for which it was not prescribed. Do not give HYCODAN to other people, even if they have the same symptoms that you have. It may harm them.
You can ask your pharmacist or healthcare provider for information about HYCODAN that is written for health professionals.

What are the ingredients in HYCODAN?
Active ingredients: hydrocodone bitartrate and homatropine methylbromide
Inactive ingredients in HYCODAN tablets: calcium phosphate dibasic, colloidal silicon dioxide, lactose, magnesium stearate, pregelatinized starch and stearic acid.
Inactive ingredients in HYCODAN oral solution: anhydrous citric acid, FD&C Red 40, methylparaben, natural and artificial cherry flavor, propylparaben, purified water, sorbitol solution, sodium citrate dihydrate and sucrose.
Manufactured by: Genus Lifesciences Inc., Allentown, PA 18102
HYCODAN® is a registered trademark of Genus Lifesciences Inc.
For more information, go to www.genuslifesciences.com or call 1-866-511-6754.

This Medication Guide has been approved by the U.S. Food and Drug Administration.

Revised: 9/2021

PRINCIPAL DISPLAY PANEL - 30 Tablet Bottle Label

NDC 64950-205-03

HYCODAN® CII
(hydrocodone bitartrate and
homatropine methylbromide)
tablets

5 mg/1.5 mg

"Dispense the accompanying Medication
Guide to each patient."

Rx Only
30 tablets

Genus
Lifesciences Inc.

PRINCIPAL DISPLAY PANEL - 473 mL Bottle Label

NDC 64950-342-47

HYCODAN®
(hydrocodone bitartrate and
homatropine methylbromide)
oral solution
CII

5 mg/1.5 mg per 5 mL

"Dispense the accompanying Medication
Guide to each patient."

Rx Only
473 mL

Genus
Lifesciences Inc.